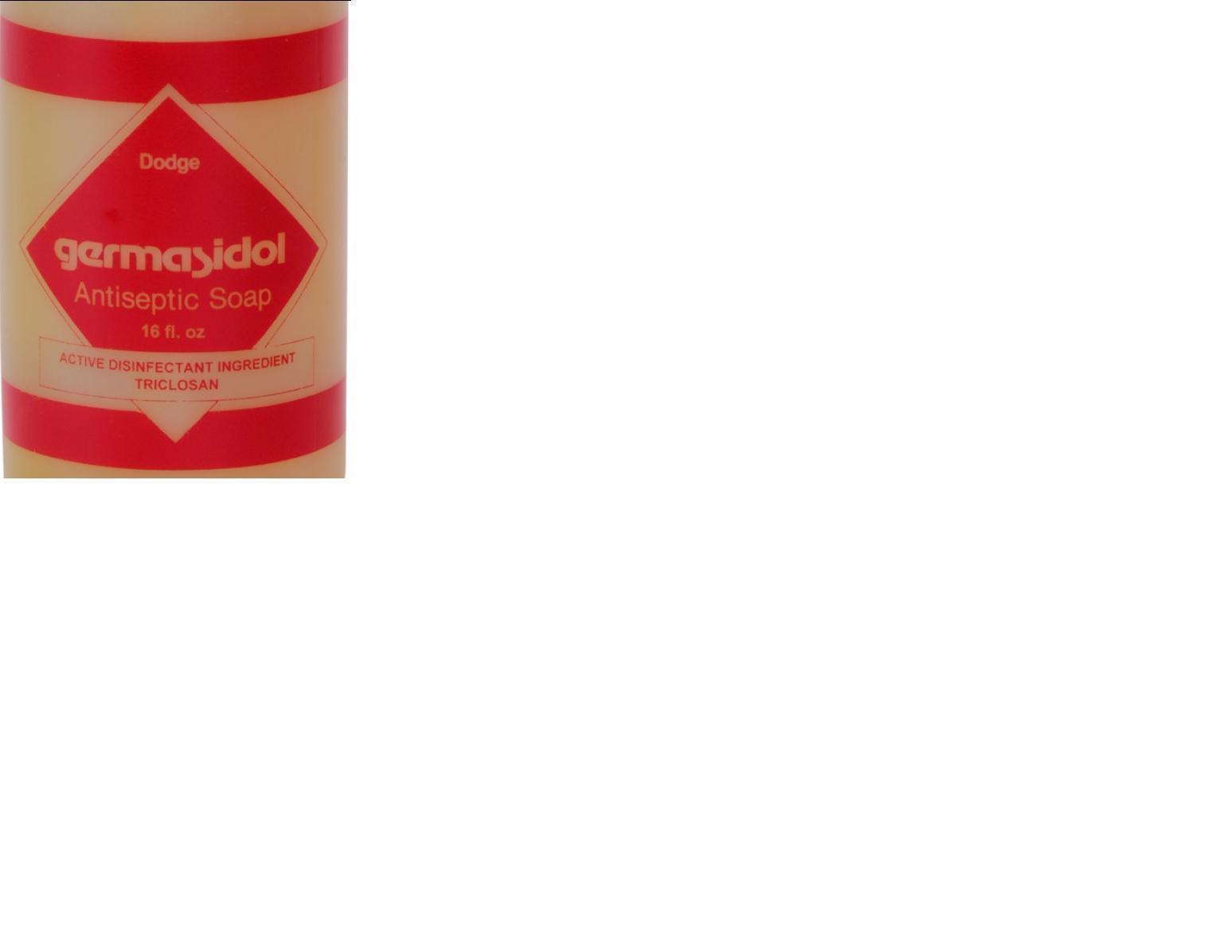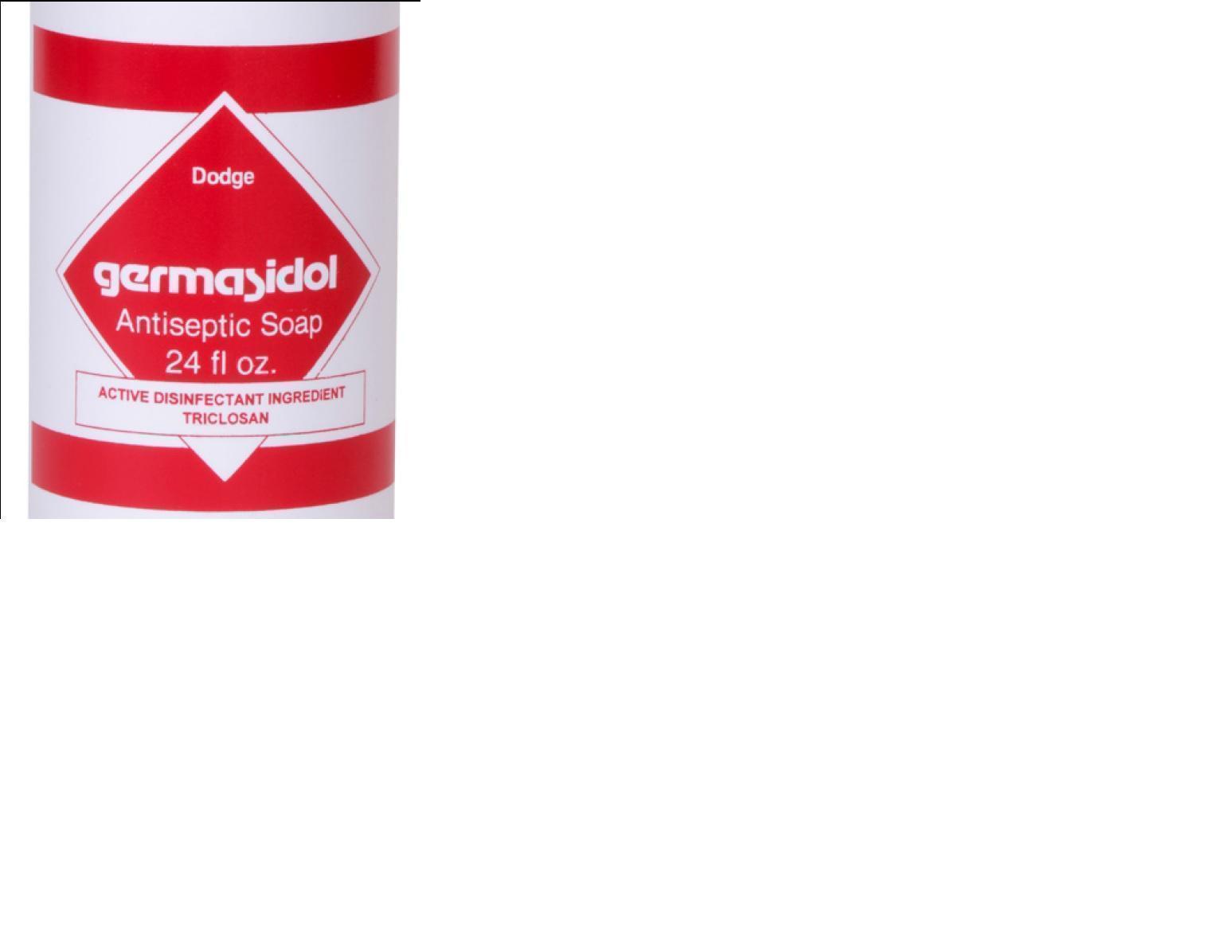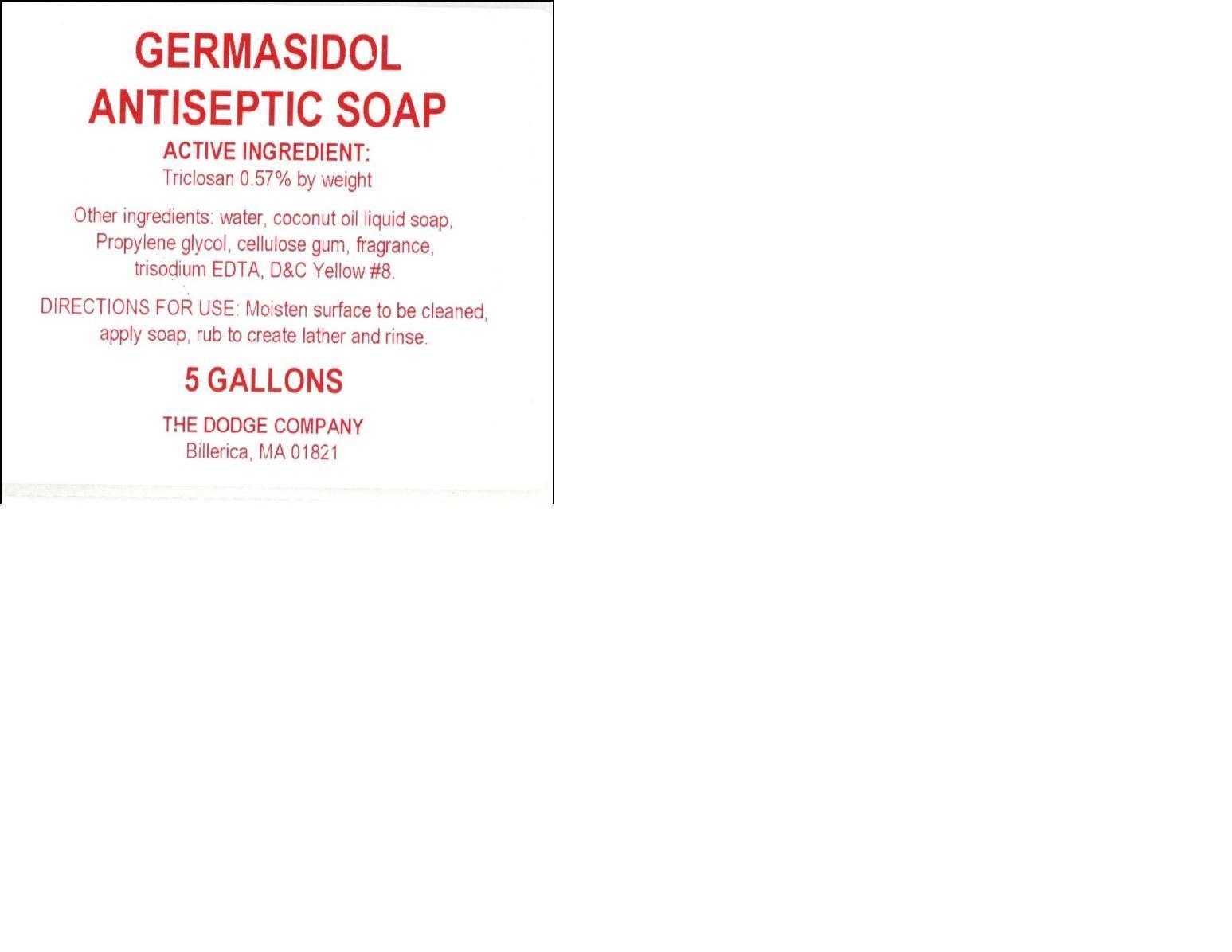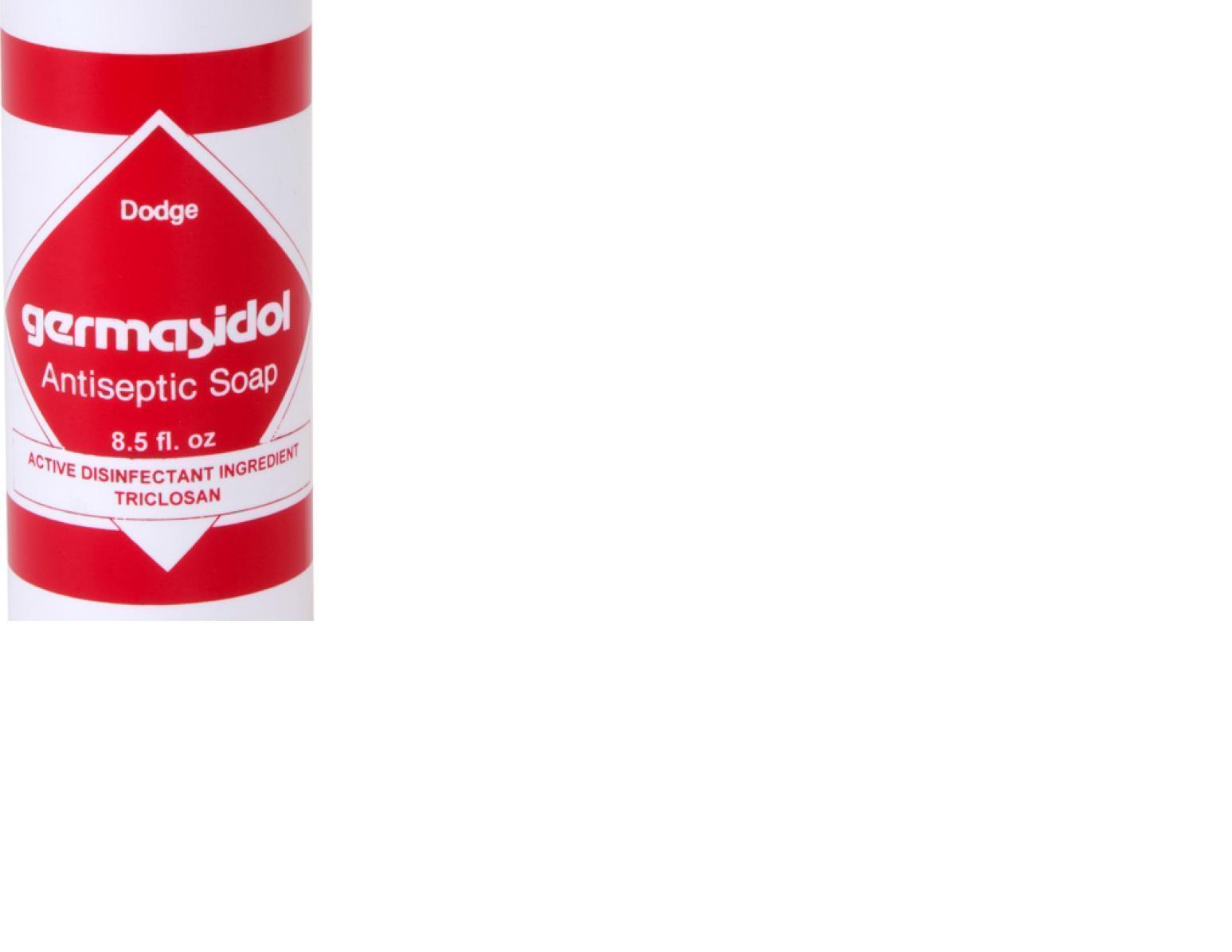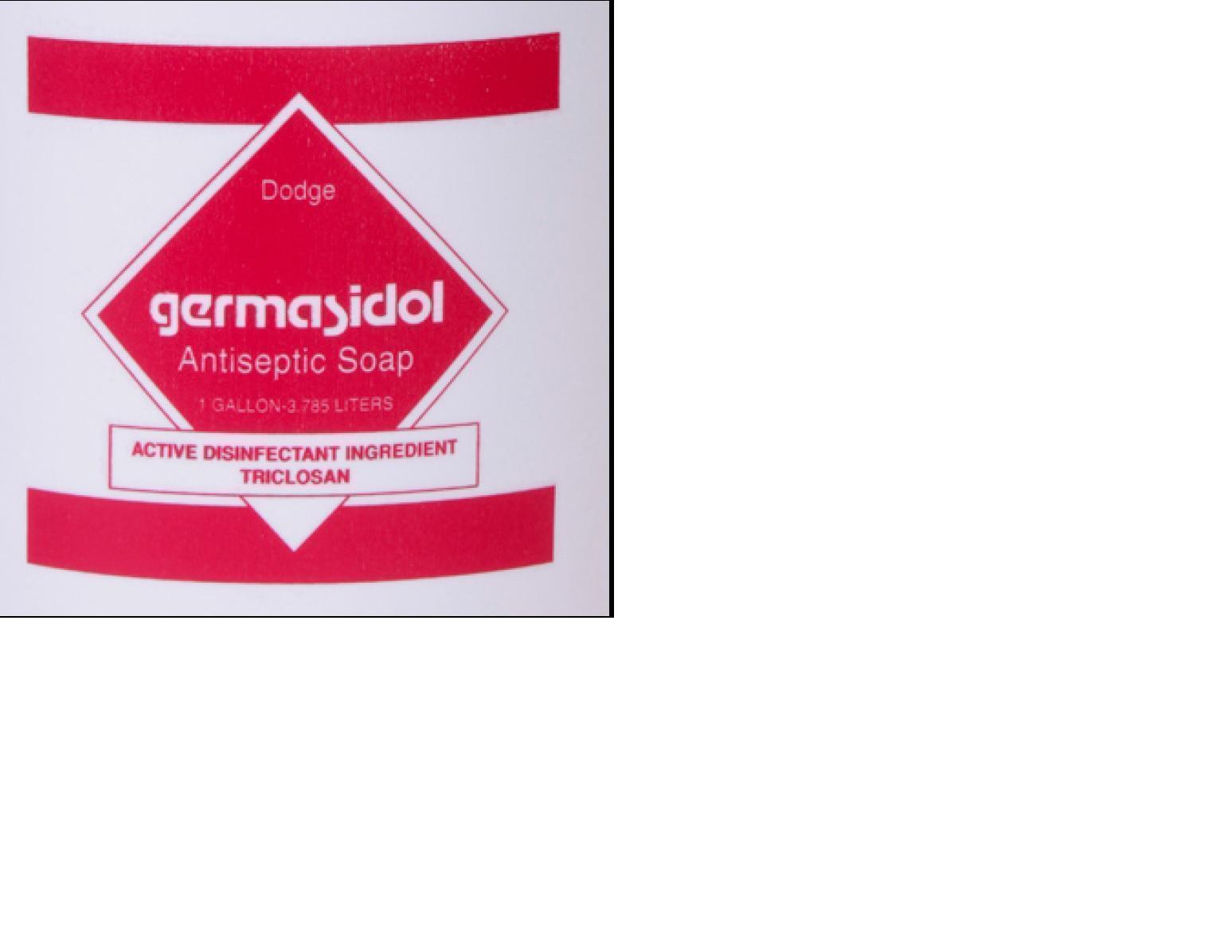 DRUG LABEL: Germasidol
NDC: 25113-333 | Form: SOAP
Manufacturer: The Dodge Company Inc.
Category: otc | Type: HUMAN OTC DRUG LABEL
Date: 20140425

ACTIVE INGREDIENTS: TRICLOSAN 0.0057 g/1 g
INACTIVE INGREDIENTS: WATER; EDETATE TRISODIUM; D&C YELLOW NO. 8; PROPYLENE GLYCOL; COCAMIDOPROPYL BETAINE; CARBOXYMETHYLCELLULOSE SODIUM

Germasidol

INDICATIONS & USAGE SECTION

Antiseptic handwash for handwashing to decrease baceria on the skin

OTC - PURPOSE SECTION

Antiseptic handwash

OTC - KEEP OUT OF REACH OF CHILDREN SECTION

Keep out of reach of children. If swallowed, get medical help or contact a Poison Control Center right away.

DOSAGE & ADMINISTRATION SECTION

Moisten surface to be cleaned, apply soap, rub to create lather, and rinse. Repeat as needed.

WARNINGS SECTION

1) For external use only.

2) Do not use in the eyes.

3) Discontinue use if irritation and redness develop. If condition persists for more than 72 hours consult a doctor

OTC - ACTIVE INGREDIENT SECTION

Triclosan

INACTIVE INGREDIENT SECTION

Carboxymethylcellulose Sodium

Carboxymethylcellulose Sodium xxxxxxxxx

Cocamidopropyl Betaine

D&C Yellow #8

Propylene Glycol

Trisodium EDTA

Water

PACKAGE LABEL.PRINCIPAL DISPLAY PANEL

Dodge Germasidol 8.5oz.jpg

PACKAGE LABEL.PRINCIPAL DISPLAY PANEL

Dodge Germasidol 16oz.jpg

PACKAGE LABEL.PRINCIPAL DISPLAY PANEL

Dodge Germasidol 24oz.jpg

PACKAGE LABEL.PRINCIPAL DISPLAY PANEL

odge Germasidol Gal.jpg

PACKAGE LABEL.PRINCIPAL DISPLAY PANEL

Dodge Germasidol 5 Gal.jpg